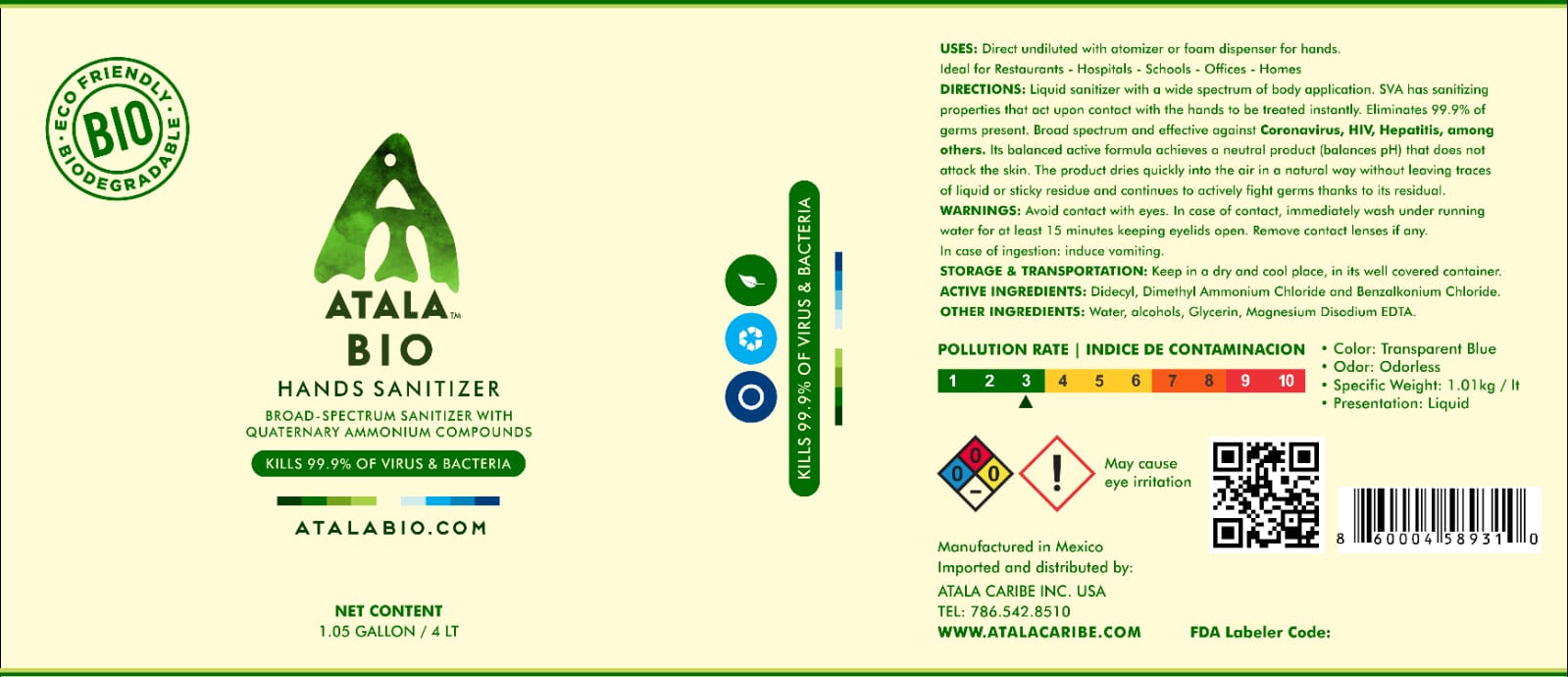 DRUG LABEL: Atala Bio Liquid Hand Sanitizer
NDC: 77396-060 | Form: LIQUID
Manufacturer: Kemix Quimica, S.A. de C.V.
Category: otc | Type: HUMAN OTC DRUG LABEL
Date: 20200917

ACTIVE INGREDIENTS: DIDECYLDIMONIUM CHLORIDE 2.5 mg/0.001 L; BENZALKONIUM CHLORIDE 1 mg/0.001 L
INACTIVE INGREDIENTS: GLYCERIN; ISOPROPYL ALCOHOL; WATER; MAGNESIUM DISODIUM EDTA; METHYL ALCOHOL

Active Ingredient(s)

DIDECYLDIMONIUM CHLORIDE 0.25% v/v. Purpose: Antiseptic

BENZALKONIUM CHLORIDE 0.01% v/v. Purpose: Antiseptic

Purpose

Antiseptic, Hand Sanitizer

Use

Hand Sanitizer to help reduce bacteria that potentially can cause disease. For use when soap and water are not available.

Warnings

For external use only. Flammable. Keep away from heat or flame. Do Not Ingest.

Do not use

- in children less than 2 months of age
- on open skin wounds

When using this product keep out of eyes, ears, and mouth. In case of contact with eyes, rinse eyes thoroughly with water.
Stop use and ask a doctor if irritation or rash occurs. These may be signs of a serious condition.
Keep out of reach of children. If swallowed, get medical help or contact a Poison Control Center right away.

Stop use and ask a doctor if irritation or rash occurs. These may be signs of a serious condition.

Keep out of reach of children. If swallowed, get medical help or contact a Poison Control Center right away.

Directions

- Place enough product on hands to cover all surfaces. Rub hands together until dry.
- Supervise children under 6 years of age when using this product to avoid swallowing.

Other information

- Store between 15-30C (59-86F)
- Avoid freezing and excessive heat above 40C (104F)

Inactive ingredients

glycerin, water, MAGNESIUM DISODIUM EDTA, ISOPROPYL ALCOHOL,METHYL ALCOHOL

Package Label - Principal Display Panel

4 L NDC: 77396-060-01